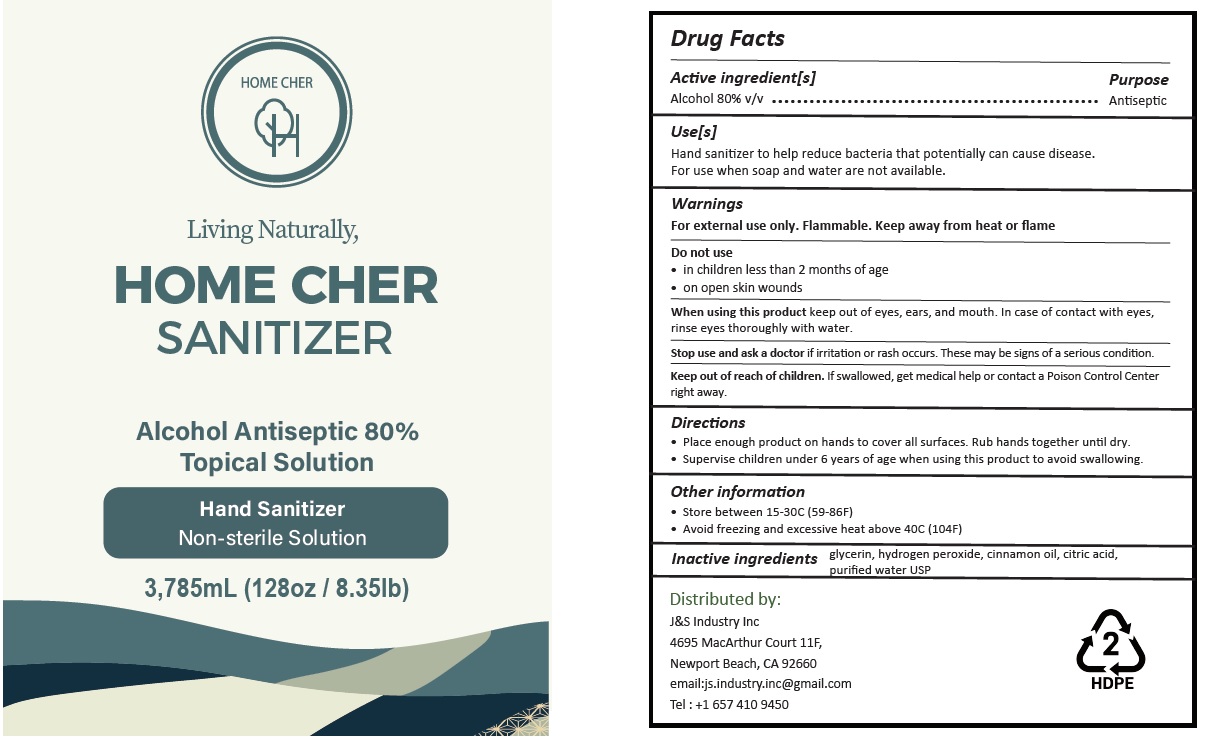 DRUG LABEL: SHIELD - HOME CHER SANITIZER
NDC: 78682-209 | Form: LIQUID
Manufacturer: J&S INDUSTRY, INC.
Category: otc | Type: HUMAN OTC DRUG LABEL
Date: 20200625

ACTIVE INGREDIENTS: ALCOHOL 80 mL/100 mL
INACTIVE INGREDIENTS: GLYCERIN; HYDROGEN PEROXIDE; CINNAMON OIL; CITRIC ACID MONOHYDRATE; WATER

HOME CHER SANITIZER

Active ingredient[s]

Alcohol 80% v/v

Purpose

Antiseptic

Use[s]

Hand sanitizer to help reduce bacteria that potentially can cause disease.

For use when soap and water are not available.

Warnings

For external use only. Flammable. Keep away from heat or flame

Do not use

• in children less than 2 months of age

• on open skin wounds

When using this product keep out of eyes, ears, and mouth. In case of contact with eyes, rinse eyes thoroughly with water.

Stop use and ask a doctor if irritation or rash occurs. These may be signs of a serious condition.

Keep out of reach of children. If swallowed, get medical help or contact a Poison Control Center right away.

Directions

• Place enough product on hands to cover all surfaces. Rub hands together until dry.

• Supervise children under 6 years of age when using this product to avoid swallowing.

Other information

• Store between 15-30C (59-86F)

• Avoid freezing and excessive heat above 40C (104F)

INACTIVE INGREDIENT

Inactive ingredients glycerin, hydrogen peroxide, cinnamon oil, citric acid, purified water USP

Living Naturally,

Topical Solution

Non-sterile Solution

Distributed by:

J&S Industry Inc.

4695 MacArthur Court 11F,

Newport Beach, CA 92660

email:js.industry.inc@gmail.com

Tel : +1 657 410 9450